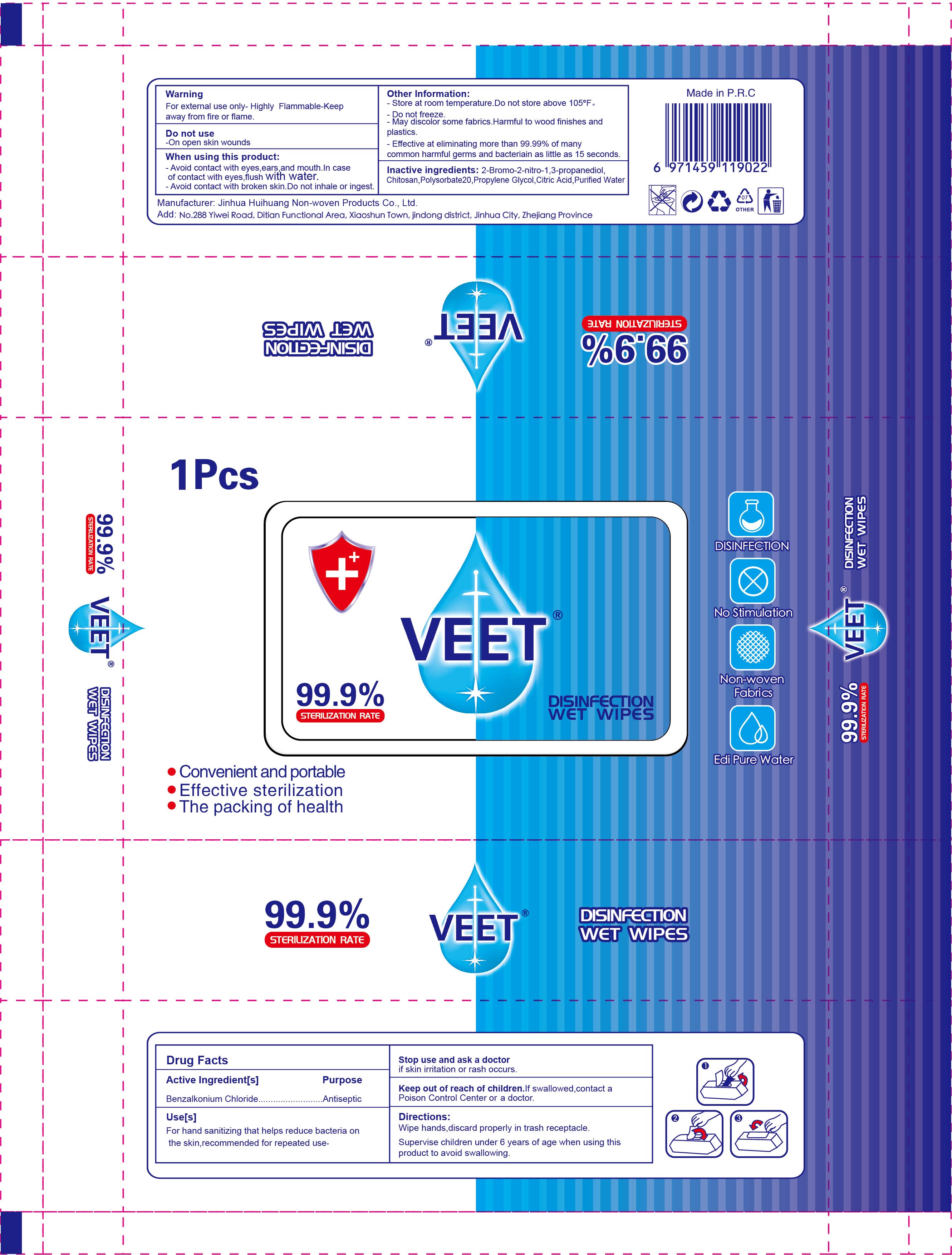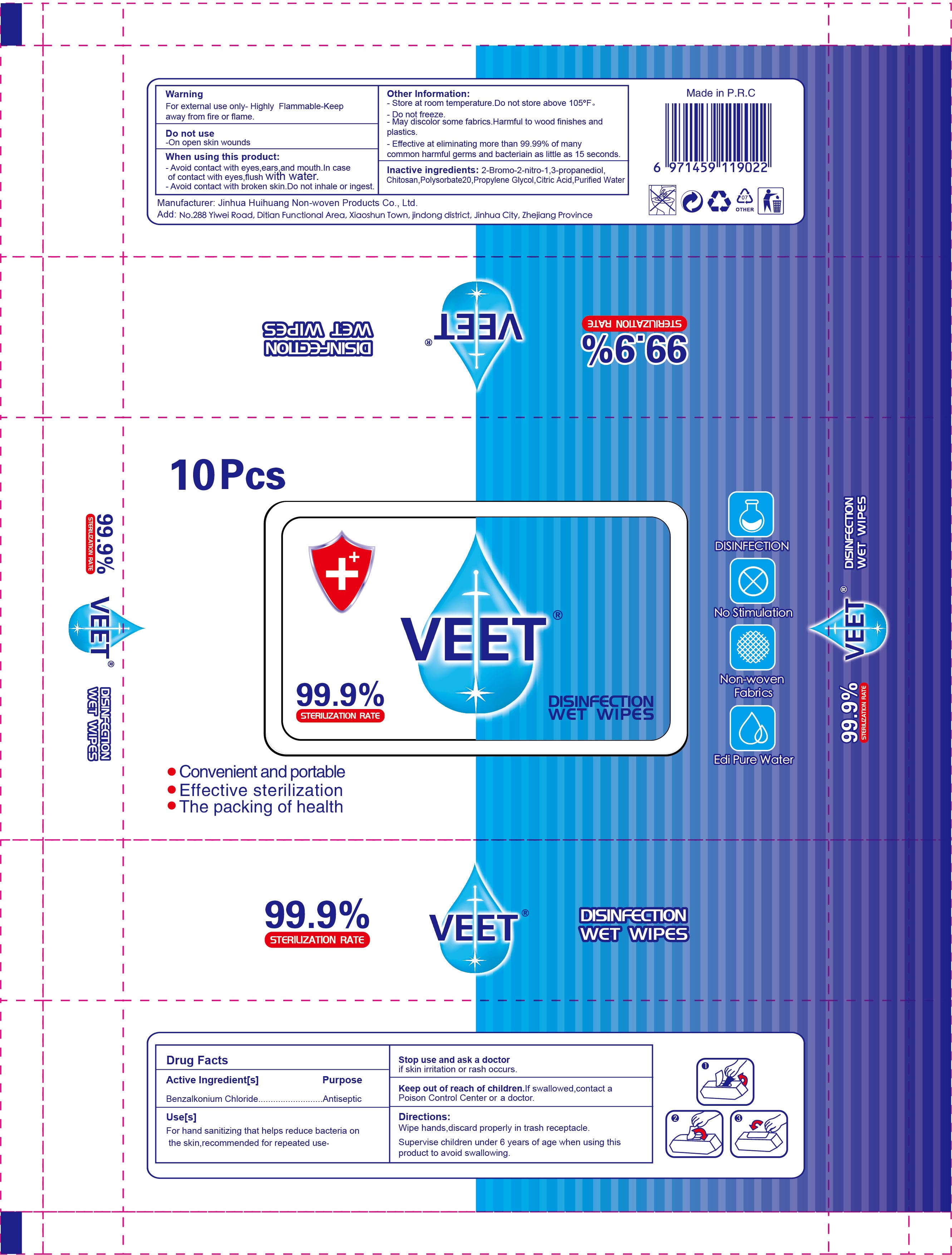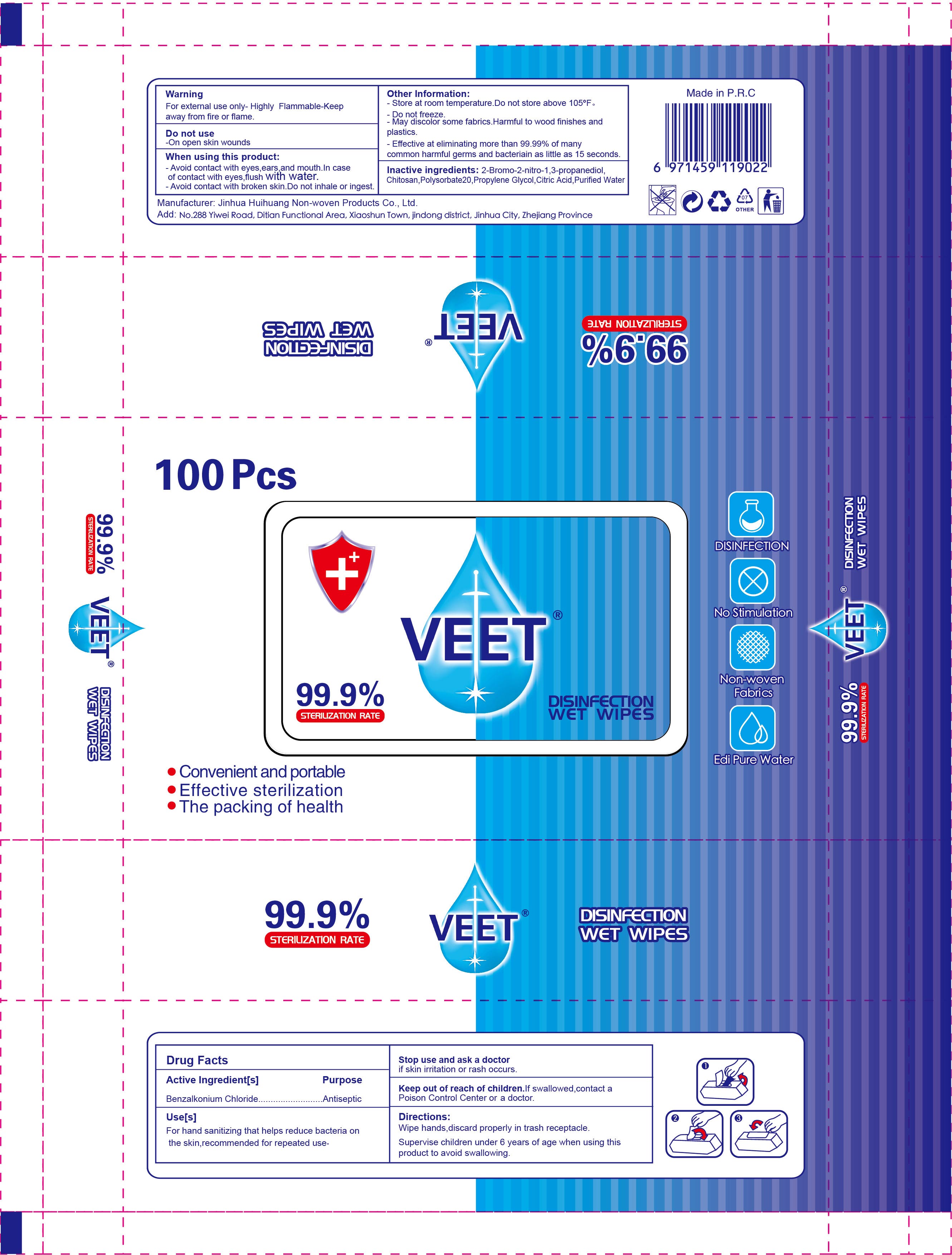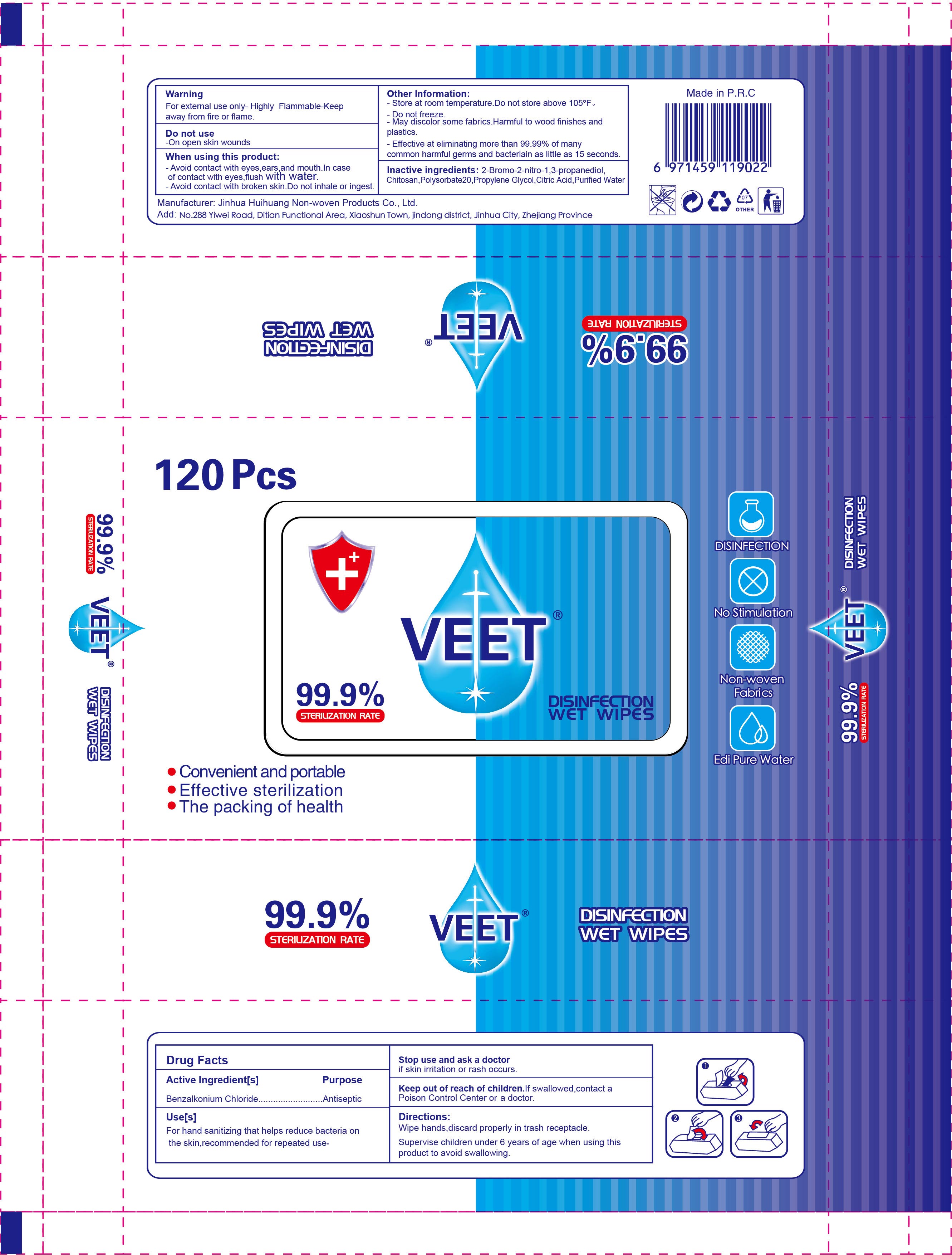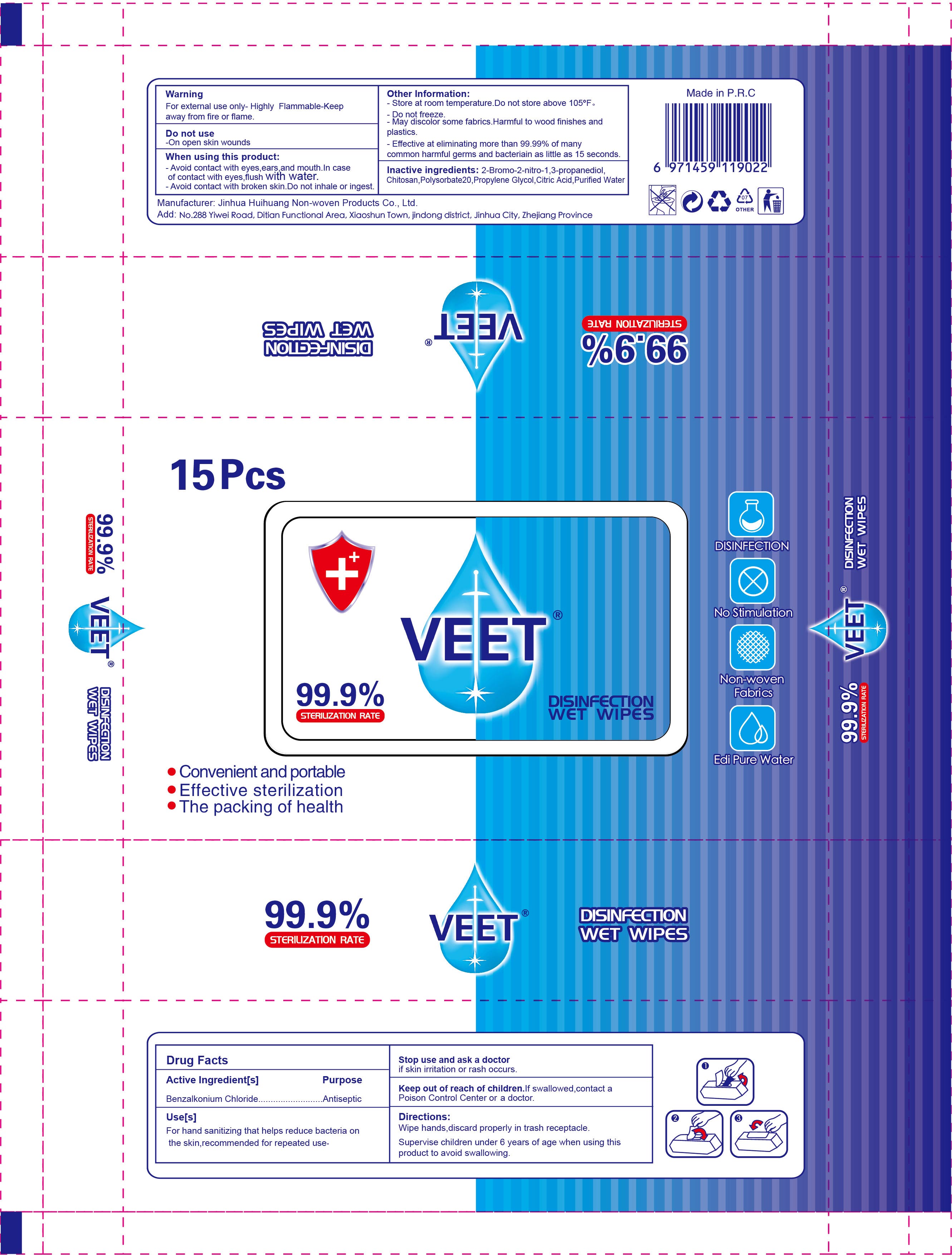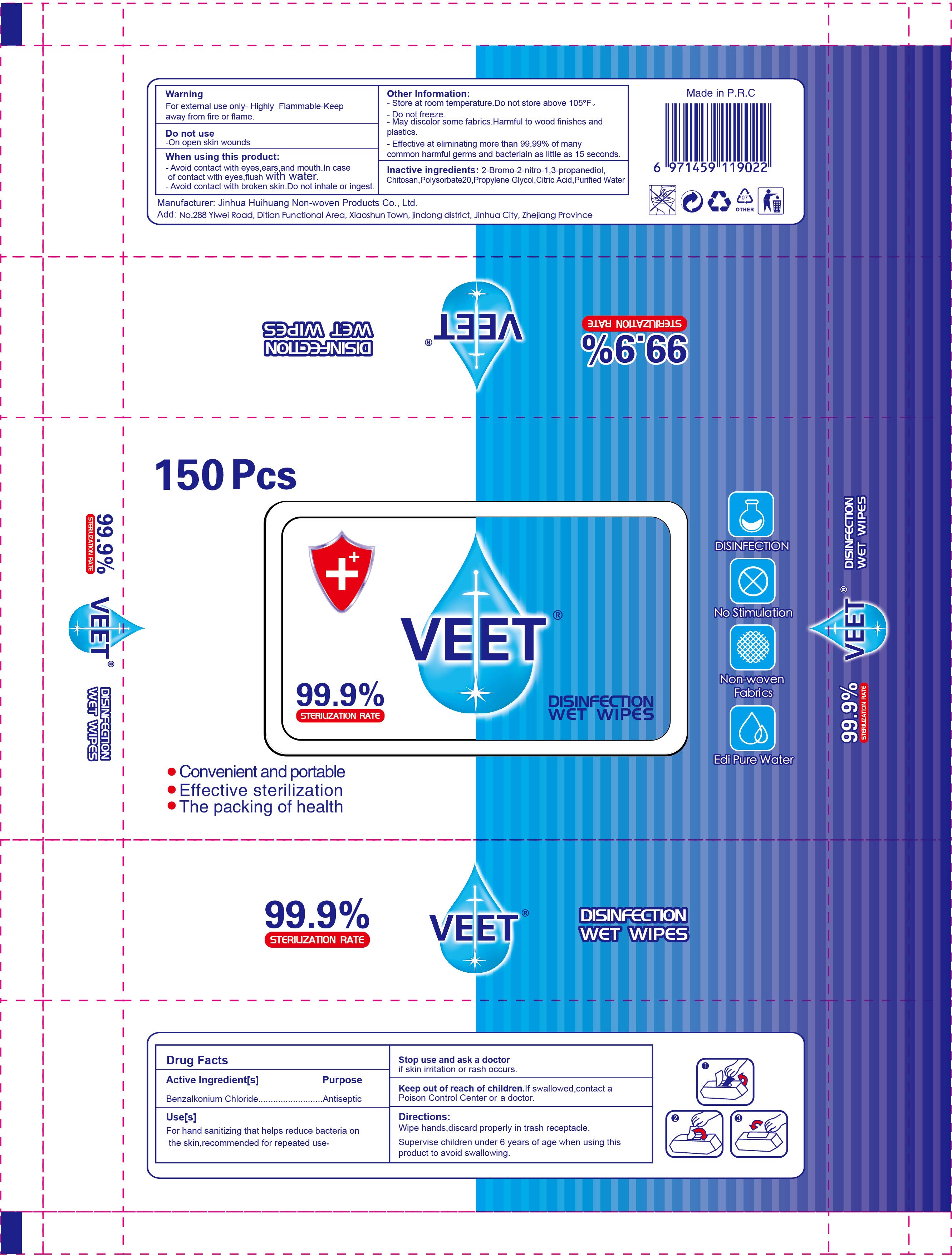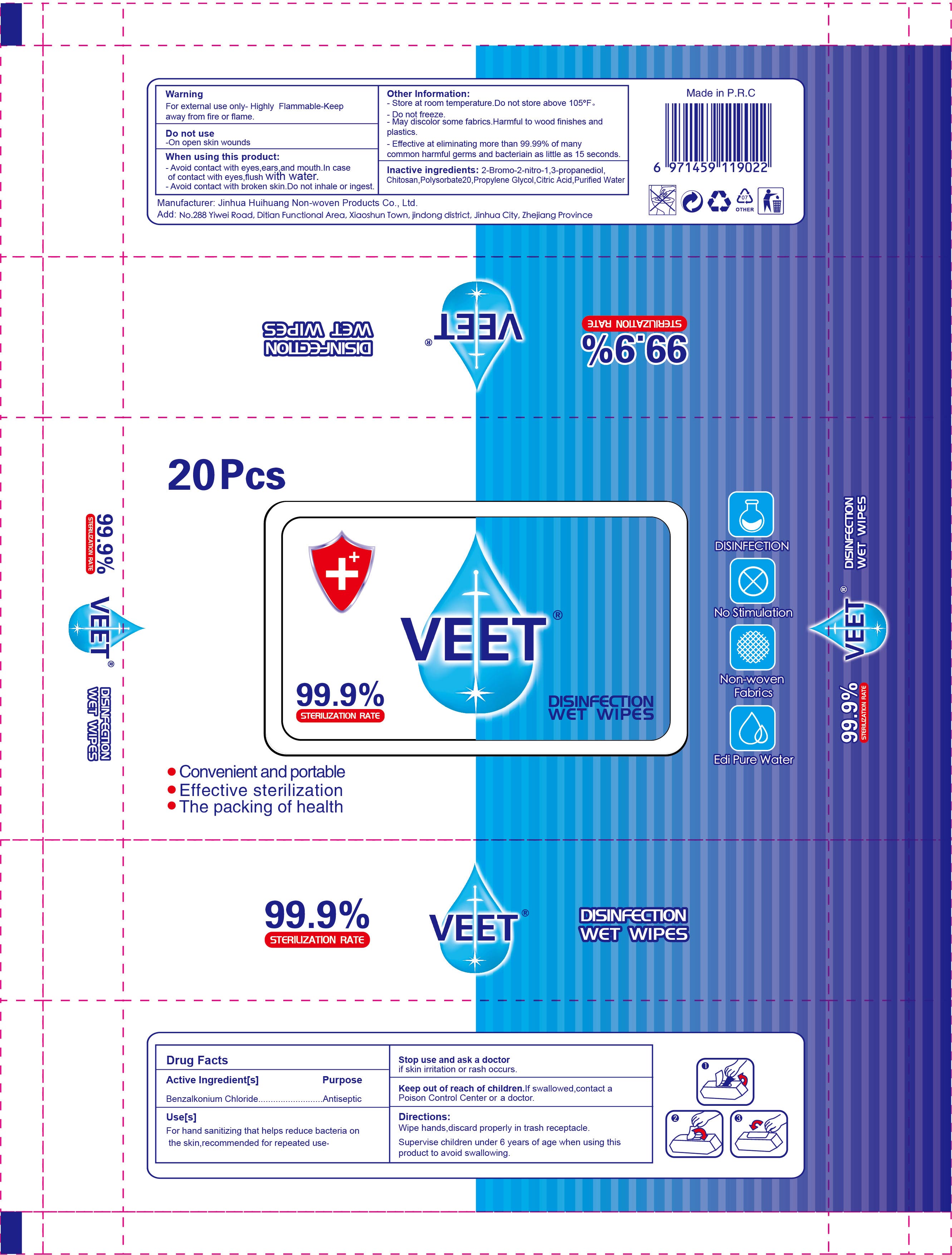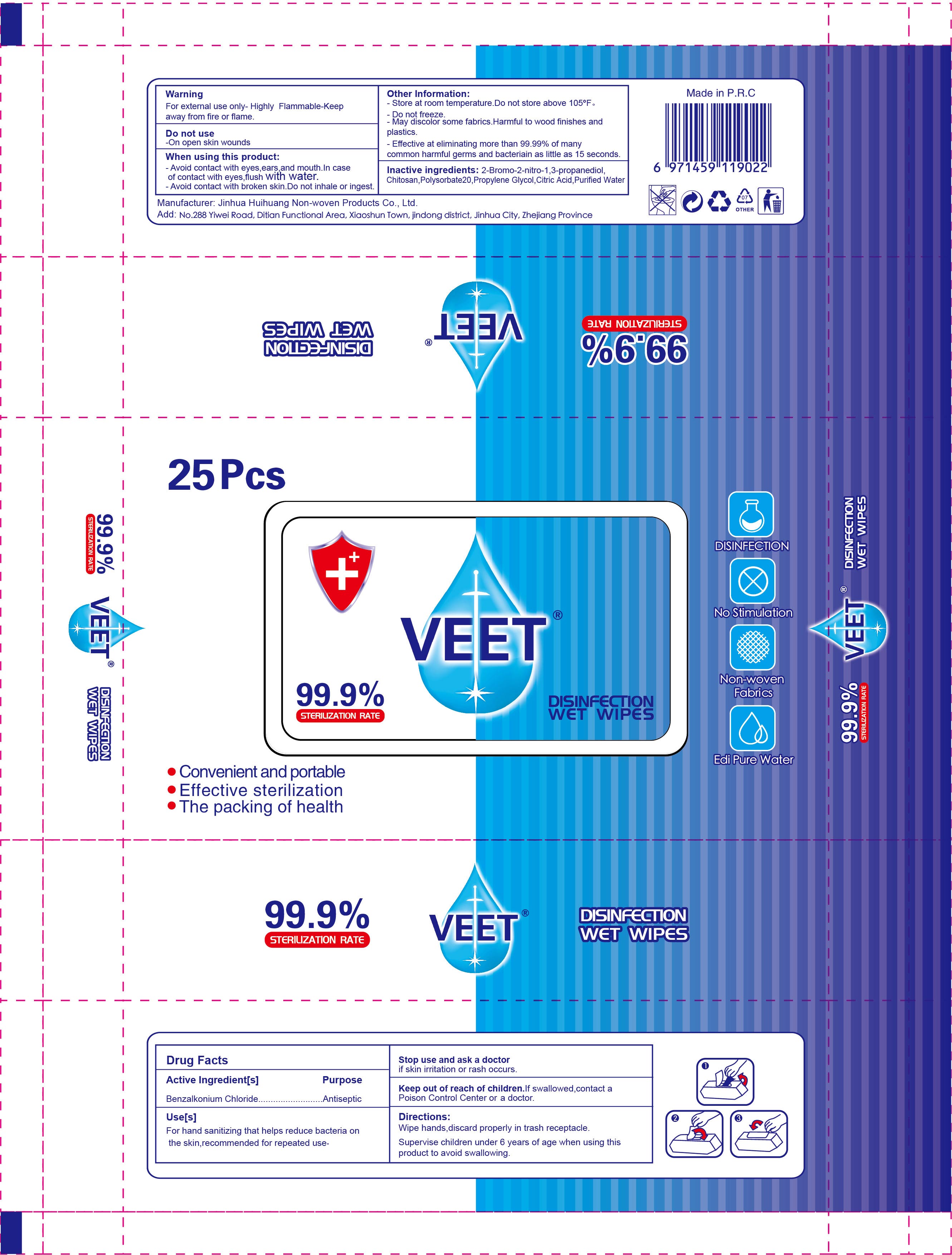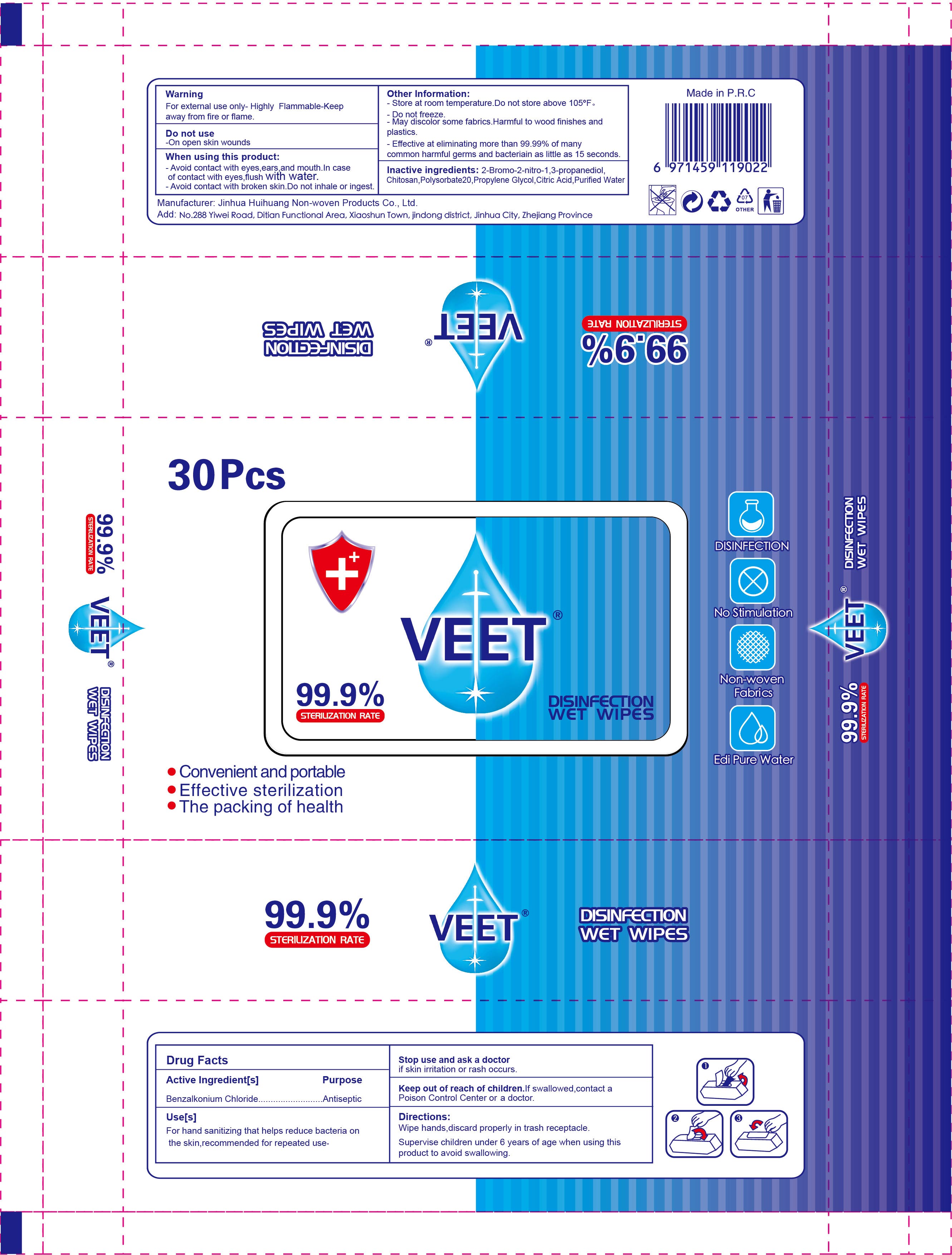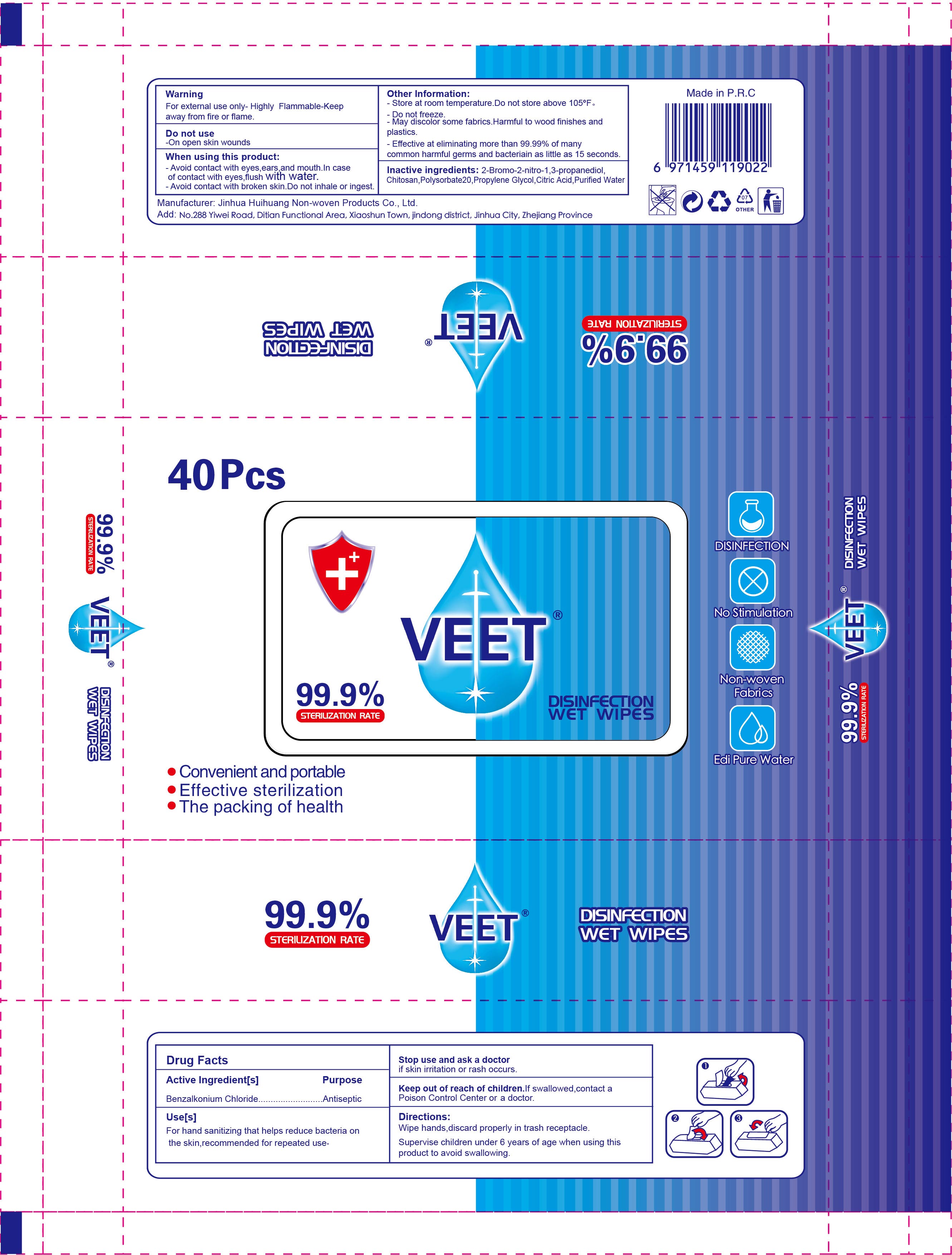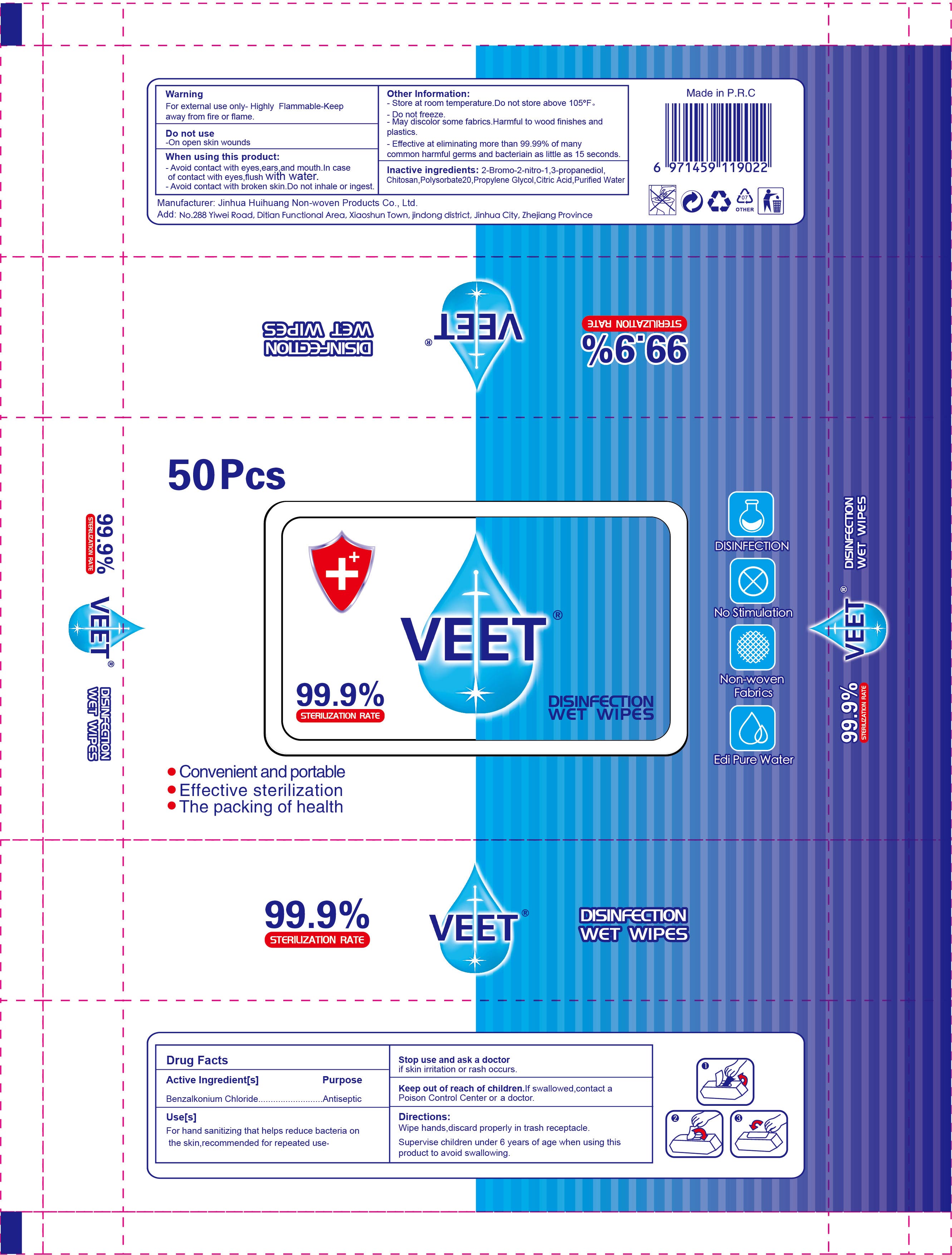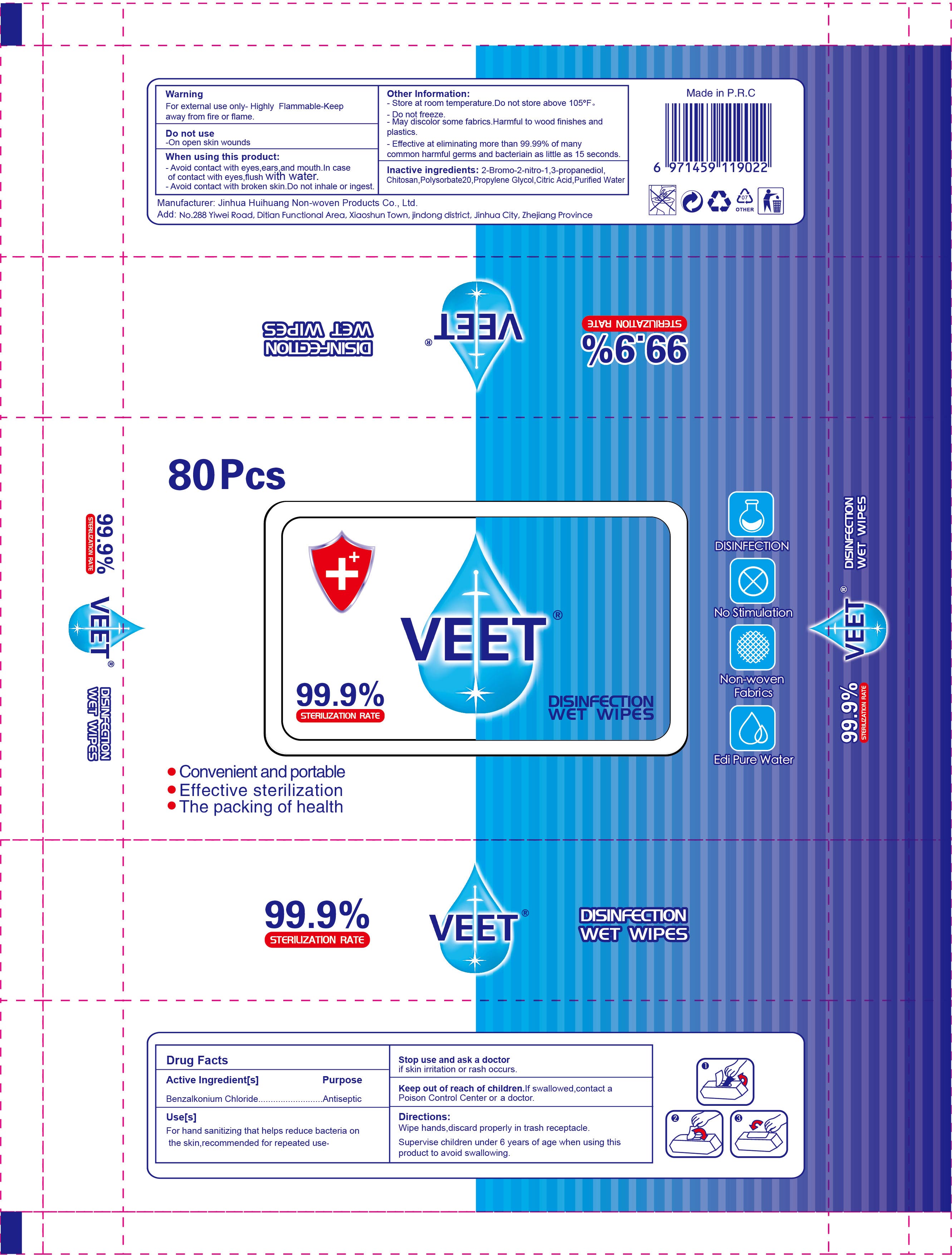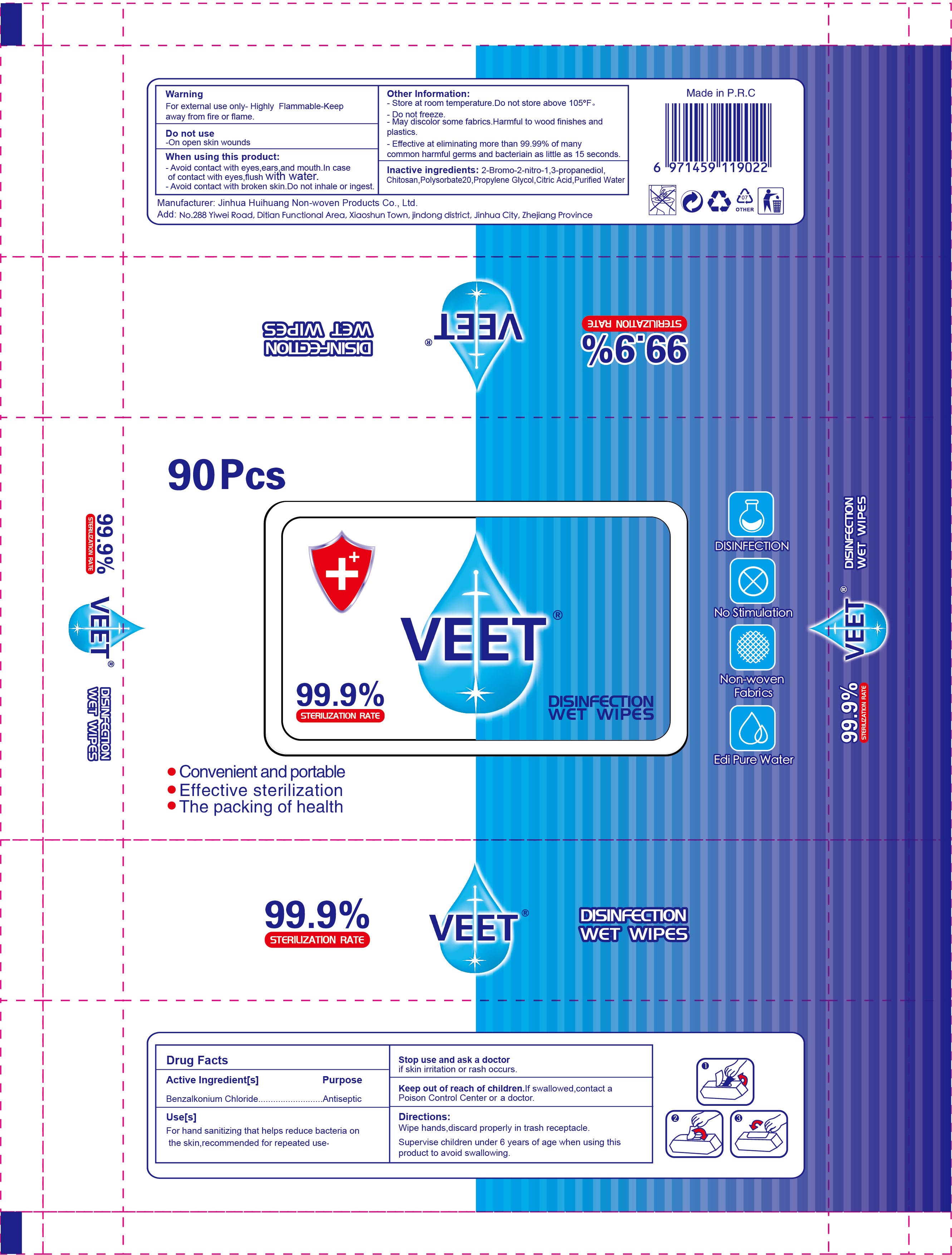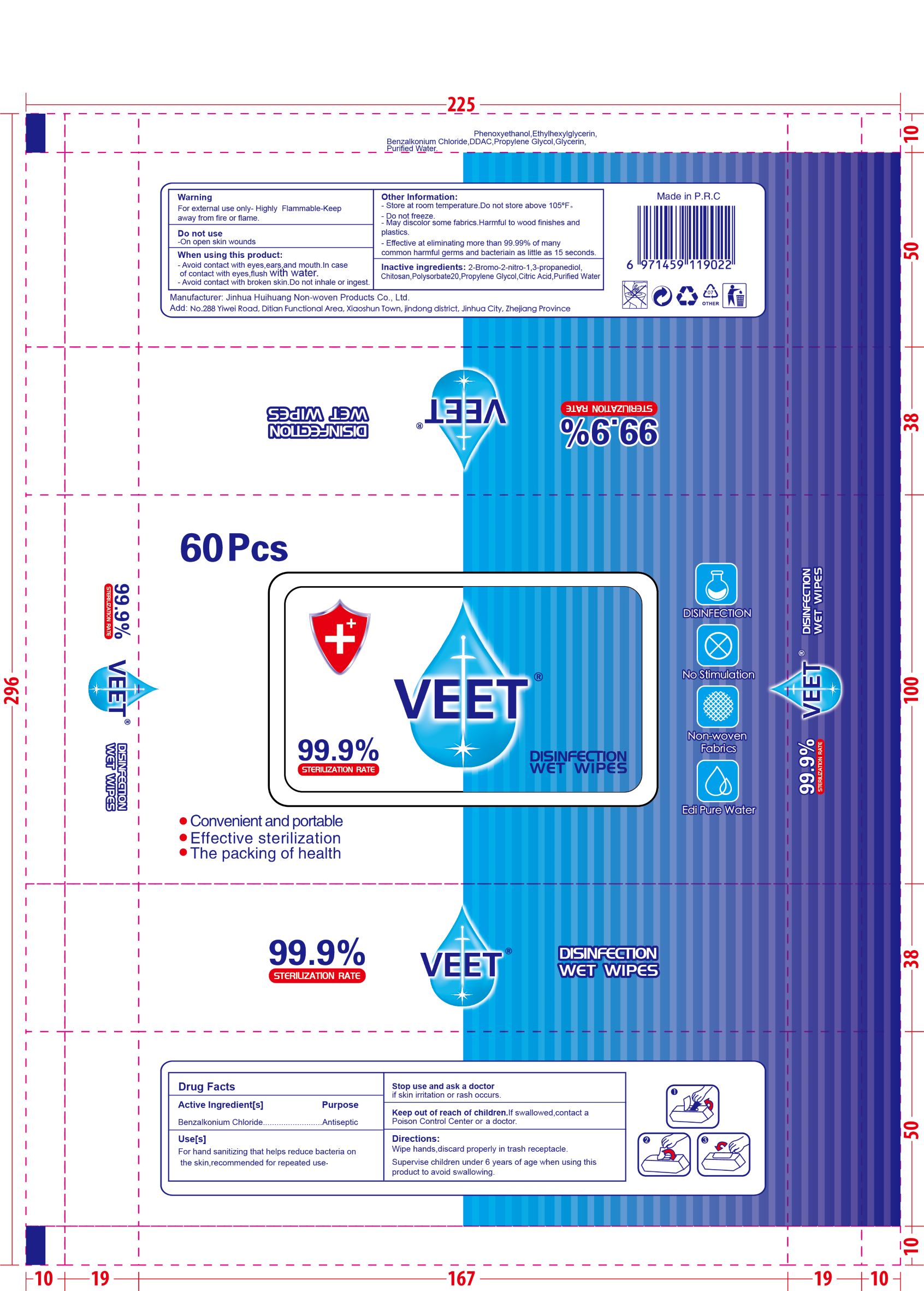 DRUG LABEL: baby wipes
NDC: 54016-005 | Form: CLOTH
Manufacturer: Jinhua Huihuang Non-woven Products Co., Ltd.
Category: otc | Type: HUMAN OTC DRUG LABEL
Date: 20200924

ACTIVE INGREDIENTS: BENZALKONIUM CHLORIDE 0.03 g/100 mL
INACTIVE INGREDIENTS: CITRIC ACID MONOHYDRATE; BRONOPOL; PROPYLENE GLYCOL; WATER; POLYSORBATE 20; POLIGLUSAM

baby wipes
60pcs NDC: 54016-005-01

Active Ingredient(s)

Benzalkonium Chloride

Purpose

Antiseptic

Use

For hand sanitizing that helps reduce bacteria on the skin, recommended for repeated use.

Warnings

- For external use only.
- Highly Flammable - Keep away from fire or flame.

Do not use

- On open skin wounds.

WHEN USING

- Avoid contact with eyes, ears, and mouth. In case of contact with eyes, flush with water.
- Avoid contact with broken skin. Do not inhale or ingest.

Stop use and ask a doctor if skin irritation or rash occurs.

Keep out of reach of children. If swallowed, contact a Poison Control Center or a doctor.

Directions

- Wipe hands, discard properly in trash receptacle.
- Supervise children under 6 years of age when using this product to avoid swallowing.

Other information

- Store at room temperature. Do not store above 105℉.
- Do not freeze
- May discolor some fabrics. Harmful to wood finishes and plastics.
- Effective at eliminating more than 99.99% of many common harmful germs and bacteriain as little as 15 seconds.

Inactive ingredients

2-Bromo-2-nitro-1,3-propanediol, Chitosan, Polysorbate 20, Propylene Glycol, Citric Acid, Purified Water.

Package Label - Principal Display Panel

NDC:54016-005-01 60PCS

NDC:54016-005-02 1PCS

NDC:54016-005-03 10PCS

NDC:54016-005-04 15PCS

NDC:54016-005-05 20PCS

NDC:54016-005-06 25PCS

NDC:54016-005-07 30PCS

NDC:54016-005-08 40PCS

NDC:54016-005-09 50PCS

NDC:54016-005-10 80PCS

NDC:54016-005-11 90PCS

NDC:54016-005-12 100PCS

NDC:54016-005-13 120PCS

NDC:54016-005-14 150PCS